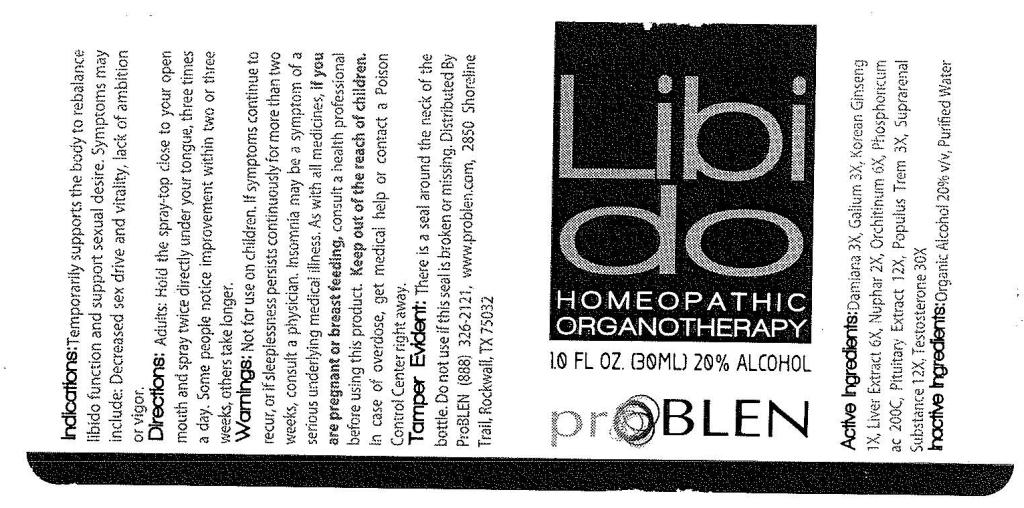 DRUG LABEL: ProBLEN Libido
NDC: 50845-0123 | Form: SPRAY
Manufacturer: Liddell Laboratories, Inc.
Category: homeopathic | Type: HUMAN OTC DRUG LABEL
Date: 20120206

ACTIVE INGREDIENTS: TURNERA DIFFUSA LEAFY TWIG 3 [hp_X]/1 mL; GALIUM APARINE 3 [hp_X]/1 mL; BOS TAURUS ADRENAL GLAND 12 [hp_X]/1 mL; BEEF LIVER 6 [hp_X]/1 mL; ASIAN GINSENG 1 [hp_X]/1 mL; PHOSPHORIC ACID 200 [hp_C]/1 mL; POPULUS TREMULOIDES LEAF 3 [hp_X]/1 mL; TESTOSTERONE 30 [hp_X]/1 mL; NUPHAR LUTEUM ROOT 2 [hp_X]/1 mL; BOS TAURUS TESTICLE 6 [hp_X]/1 mL; BOS TAURUS PITUITARY GLAND 12 [hp_X]/1 mL
INACTIVE INGREDIENTS: WATER; ALCOHOL

ProBLEN Libido

ACTIVE INGREDIENT

ACTIVE INGREDIENTS: Damiana 3X, Galium aparine 3X, Glandula suprarenalis bovinum 12X, Hepar bovinum 6X, Korean ginseng 1X, Nuphar luteum 2X, Orchitinum bovinum 6X, Phosphoricum acidum 200C, Pituitary bovinum 12X, Populus tremuloides 3X, Testosterone 30X.

PURPOSE

INDICATIONS: Temporarily supports the body to rebalance libido function and support sexual desire. Symptoms may include: Decreased sex drive and vitality, lack of ambition or vigor.

WARNINGS

WARNINGS: Not for use on children. If symptoms continue to recur, or if sleeplessness persists continuously for more than two weeks, consult a physician. Insomnia may be a symptom of a serious underlying medical illness.

As with all medicines, if you are pregnant or breast feeding, consult a health professional before using this product.

Keep out of reach of children. In case of overdose, get medical help or contact a Poison Control Center right away.

TAMPER EVIDENT: There is a seal around the neck of the bottle. Do not use if this seal is broken or missing.

DOSAGE AND ADMINISTRATION

DIRECTIONS: Adults: Hold the spray-top close to your open mouth and spray twice directly under your tongue, three times a day. Some people notice improvement within two or three weeks, others take longer.

INACTIVE INGREDIENT

INACTIVE INGREDIENTS: Organic alcohol 20% v/v, Purified water.

KEEP OUT OF REACH OF CHILDREN. In case of overdose, get medical help or contact a Poison Control Center right away.

INDICATIONS AND USAGE

INDICATIONS: Temporarily supports the body to rebalance libido function and support sexual desire. Symptoms may include: Decreased sex drive and vitality, lack of ambition or vigor.

QUESTIONS

Distributed By:

ProBLEN

(888) 326-2121

www.problen.com

2850 Shoreline Trail

Rockwall, TX 75032

PACKAGE LABEL

Libido

HOMEOPATHIC ORGANOTHERAPY

1.0 FL OZ (30 ML)

proBLEN